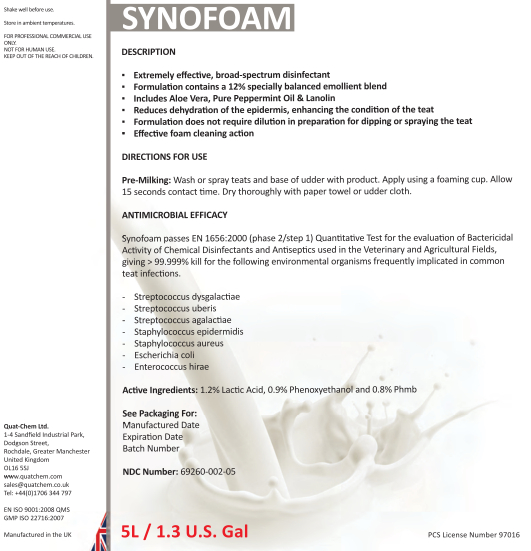 DRUG LABEL: Synofoam
NDC: 69260-002 | Form: LIQUID
Manufacturer: Quat-Chem Ltd.
Category: animal | Type: OTC ANIMAL DRUG LABEL
Date: 20160316

ACTIVE INGREDIENTS: DIDECYLDIMONIUM CHLORIDE 0.7 g/1 L; BENZALKONIUM CHLORIDE 0.5 1/1 L

Synofoam

Synofoam

Shake well before use.
Store in ambient temperatures.
FOR PROFESSIONAL COMMERCIAL USE ONLY.
NOT FOR HUMAN USE.
KEEP OUT OF THE REACH OF CHILDREN.

Quat-Chem Ltd.
1-4 Sandfield Industrial Park,
Dodgson Street,
Rochdale, Greater Manchester
United Kingdom
OL16 5SJ
www.quatchem.com
sales@quatchem.co.uk
Tel: +44(0)1706 344 797

EN ISO 9001:2008 QMS
GMP ISO 22716:2007

Manufactured in the UK

DESCRIPTION
▪ Extremely effective, broad-spectrum disinfectant
▪ Formulation contains a 12% specially balanced emollient blend
▪ Includes Aloe Vera, Pure Peppermint Oil & Lanolin
▪ Reduces dehydration of the epidermis, enhancing the condition of the teat
▪ Formulation does not require dilution in preparation for dipping or spraying the teat
▪ Effective foam cleaning action

DIRECTIONS FOR USE
Pre-Milking: Wash or spray teats and base of udder with product. Apply using a foaming cup. Allow 15 seconds contact time. Dry thoroughly with paper towel or udder cloth.

ANTIMICROBIAL EFFICACY
Synofoam passes EN 1656:2000 (phase 2/step 1) Quantitative Test for the evaluation of Bactericidal Activity of Chemical Disinfectants and Antiseptics used in the Veterinary and Agricultural Fields, giving > 99.999% kill for the following environmental organisms frequently implicated in common teat infections.
- Streptococcus dysgalactiae
- Streptococcus uberis
- Streptococcus agalactiae
- Staphylococcus epidermidis
- Staphylococcus aureus
- Escherichia coli
- Enterococcus hirae
Active Ingredients: 1.2% Lactic Acid, 0.9% Phenoxyethanol and 0.8% Phmb
See Packaging For:
Manu Manufactured Date
Expiration Date
Batch Numbe

NDC Number: